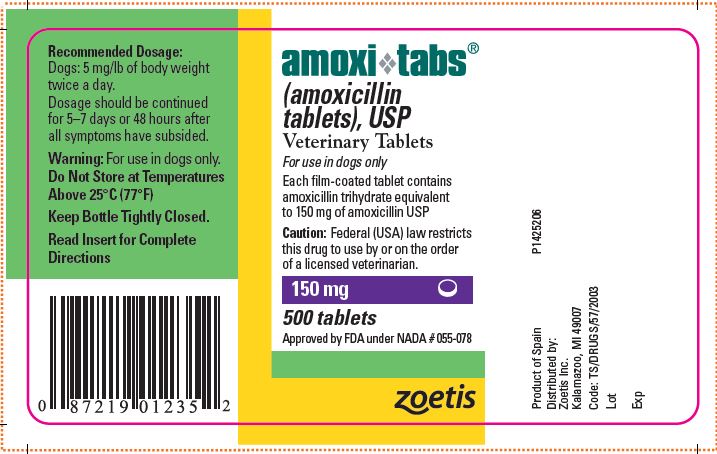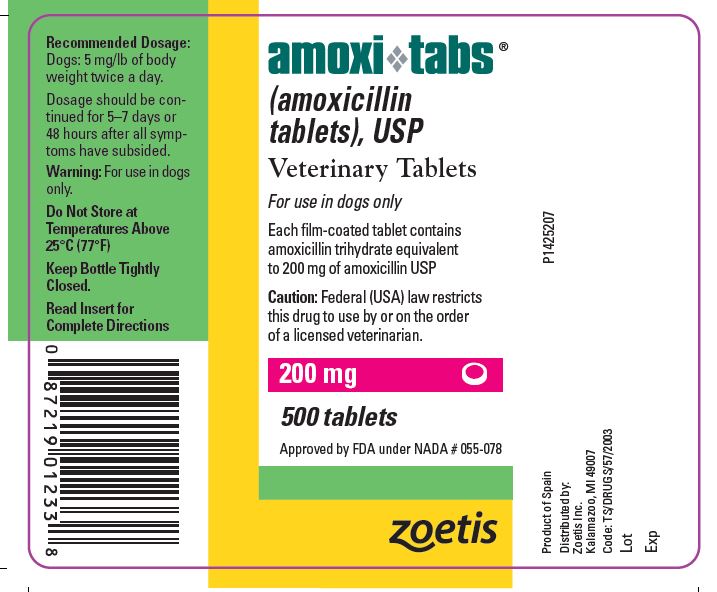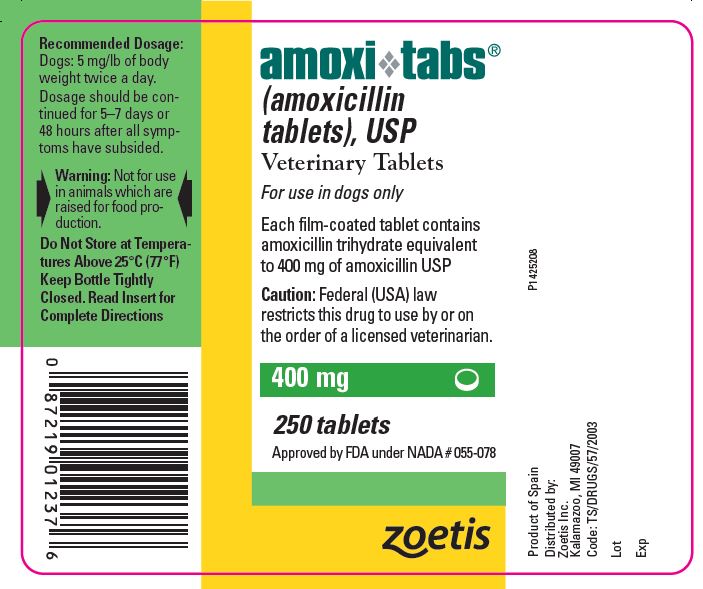 DRUG LABEL: Amoxi-Tabs
NDC: 54771-8007 | Form: TABLET, FILM COATED
Manufacturer: Zoetis Inc.
Category: animal | Type: PRESCRIPTION ANIMAL DRUG LABEL
Date: 20241114

ACTIVE INGREDIENTS: AMOXICILLIN 150 mg/1 1

amoxi❖tabs®
(amoxicillin tablets), USP
Veterinary Tablets
For use in dogs and cats

CAUTION

Federal law restricts this drug to use by or on the order of a licensed veterinarian.

DESCRIPTION

Amoxi-Tabs (amoxicillin tablets) is a semisynthetic antibiotic with a broad spectrum of activity. It provides bactericidal activity against a wide range of common gram-positive and gram-negative pathogens. Chemically, it is D(-)-α-amino-p-hydroxybenzyl penicillin trihydrate.

CLINICAL PHARMACOLOGY

Amoxi-Tabs is stable in the presence of gastric acid and may be given without regard to meals. It is rapidly absorbed after oral administration. It diffuses readily into most body tissues and fluids with the exception of brain and spinal fluid, except when meninges are inflamed. Most of the amoxicillin is excreted unchanged in the urine.

Amoxicillin is similar to ampicillin in its bactericidal action against susceptible organisms. It acts through the inhibition of biosynthesis of cell wall mucopeptide. In vitro and/or in vivo studies have demonstrated the susceptibility of most strains of the following gram-positive and gram-negative bacteria: a- and b-haemolytic streptococci, nonpenicillinaseproducing staphylococci, Streptococcus faecalis, Escherichia coli, and Proteus mirabilis. Because it does not resist destruction by penicillinase, it is not effective against penicillinase-producing bacteria, particularly resistant staphylococci. All strains of Pseudomonas and most strains of Klebsiella and Enterobacter are resistant.

INDICATIONS AND USAGE

Dogs: Amoxi-Tabs are indicated in the treatment of susceptible strains of the organisms causing the following infections:

Respiratory tract infections (tonsillitis, tracheobronchitis) due to Staphylococcus aureus, Streptococcus spp., E. coli, and Proteus mirabilis. Genitourinary tract infections (cystitis) due to Staphylococcus aureus, Streptococcus spp., E. coli, and Proteus mirabilis.

Genitourinary tract infections(cystitis) due to Staphylococcus aureus, Streptococcus spp., E. coli, and Proteus mirabilis.

Gastrointestinal tract infections (bacterial gastroenteritis) due to Staphylococcus aureus, Streptococcus spp., E. coli, and Proteus mirabilis. Bacterial dermatitis due to Staphylococcus aureus, Streptococcus spp., and Proteus mirabilis.

Bacterial dermatitis due to Staphylococcus aureus, Streptococcus spp., and Proteus mirabilis.

Soft tissue infections (abscesses, lacerations, and wounds) due to Staphylococcus aureus, Streptococcus spp., E. coli, and Proteus mirabilis.

Cats:Amoxi-Tabs are indicated in the treatment of susceptible strains of the organisms causing the following infections:

Upper respiratory tract infections due to Staphylococcus aureus, Streptococcus spp., and E. coli.

Genitourinary tract infections (cystitis) due to Staphylococcus aureus, Streptococcus spp., E. coli, and Proteus mirabilis.

Gastrointestinal tract infections due to E. coli. Skin and soft tissue infections (abscesses, lacerations, and wounds) due to Staphylococcus aureus, Streptococcus spp., E. coli, and Pasteurella multocida.

As with all antibiotics, appropriate in vitro culturing and susceptibility testing of samples taken before treatment should be conducted.

CONTRAINDICATIONS

The use of this drug is contraindicated in animals with a history of an allergic reaction to penicillin.

WARNING

For use in dogs and cats only.

ADVERSE REACTIONS

Amoxicillin is a semisynthetic penicillin and has the potential for producing allergic reactions. If an allergic reaction occurs, administer epinephrine and/or steroids.

DOSAGE AND ADMINISTRATION

Dogs: The recommended dosage is 5 mg/lb of body weight twice a day.

Cats: The recommended dosage is 50 mg (5–10 mg/lb) once a day.

Dosage should be continued for 5–7 days or 48 hours after all symptoms have subsided. If no improvement is seen in 5 days, review diagnosis and change therapy.

STORAGE AND HANDLING

Do Not Store at Temperatures Above 25°C (77°F)

Keep Bottle Tightly Closed.

HOW SUPPLIED

Amoxi-Tabs are supplied in 5 strengths: 50 mg, 100 mg, 150 mg, and 200 mg in bottles of 500 tablets; 400 mg in bottles of 250 tablets.

Approved by FDA under NADA # 055-078
Approved by FDA under NADA # 055-081
zoetis
Distributed by:
Zoetis Inc.
Kalamazoo, MI 49007
P1523357
Revised: January 2020